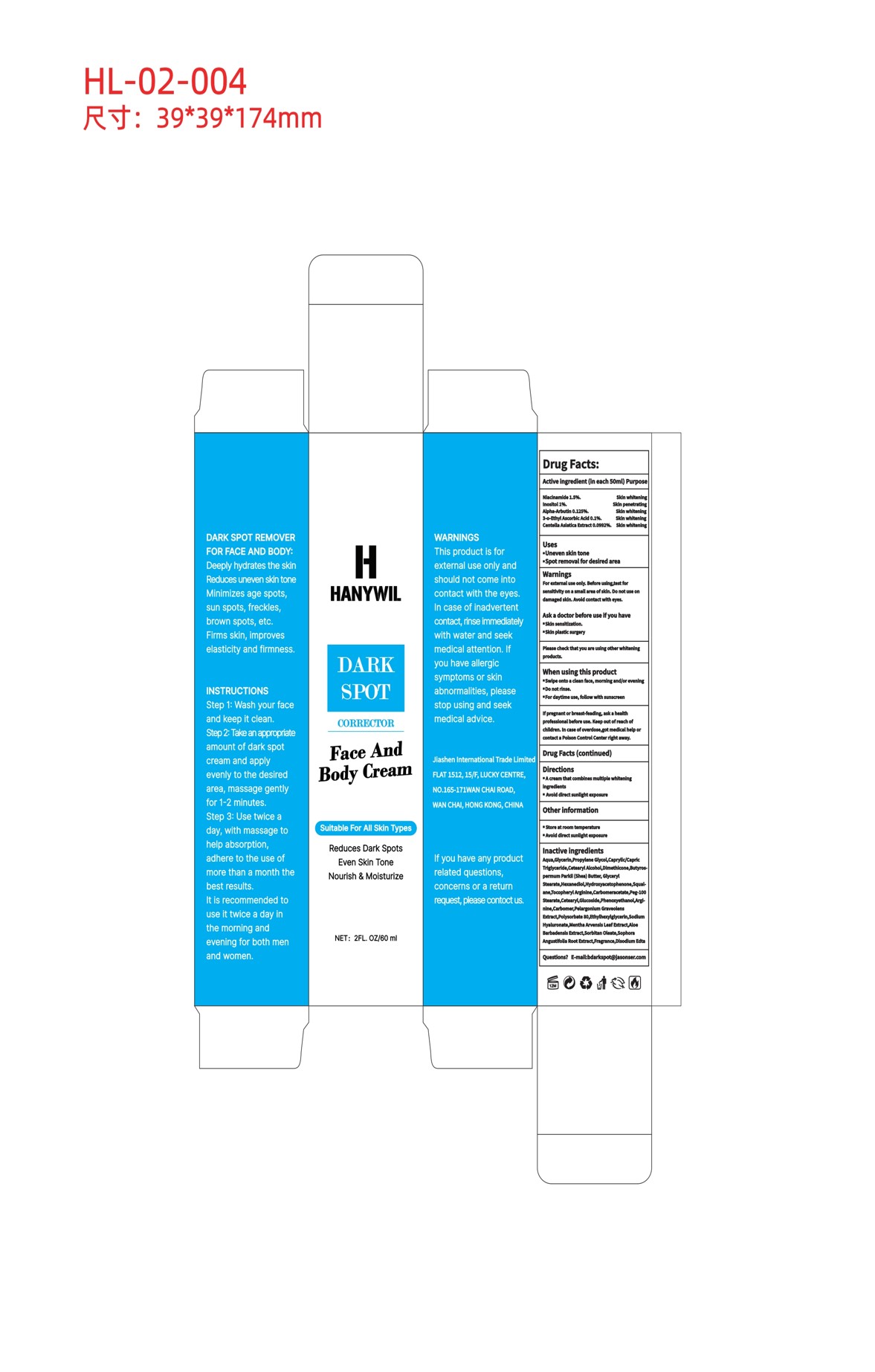 DRUG LABEL: HANYWIL-DARK SPOT
NDC: 84867-003 | Form: CREAM
Manufacturer: Jiashen International Trading Co., Ltd.
Category: otc | Type: HUMAN OTC DRUG LABEL
Date: 20241110

ACTIVE INGREDIENTS: ALPHA-ARBUTIN 125 mg/50 mL; INOSITOL 1000 mg/50 mL; 3-O-ETHYL ASCORBIC ACID 100 mg/50 mL; CENTELLA ASIATICA TRITERPENOIDS 99.2 mg/50 mL; NIACINAMIDE 1500 mg/50 mL
INACTIVE INGREDIENTS: GLYCERIN; PROPYLENE GLYCOL; DIMETHICONE 350; BUTYROSPERMUM PARKII (SHEA) BUTTER; CHRYSANTHELLUM INDICUM TOP; CARBOMER; FRAGRANCE 13576; GLYCERYL STEARATE/PEG-100 STEARATE; SOPHORA FLAVESCENS ROOT; CAPRYLIC/CAPRIC TRIGLYCERIDE; PORTULACA OLERACEA LEAF; PELARGONIUM GRAVEOLENS LEAF OIL; ETHYLHEXYLGLYCERIN; ALOE BARBADENSIS LEAF EXTRACT; SQUALANE; 1,2-HEXANEDIOL; CETEARYL GLUCOSIDE; EDETATE DISODIUM; ALPHA-TOCOPHEROL ACETATE; HYDROXYACETOPHENONE; HAMAMELIS VIRGINIANA TOP WATER; CETEARYL ALCOHOL; MENTHA ARVENSIS LEAF; PHENOXYETHANOL

ACTIVE INGREDIENT

NIACINAMIDE 1.5%/50ml
INOSITOL 1%/ml
ALPHA-ARBUTIN 0.15%/ml

CENTELLA ASIATICA EXTRACT 0.125%/ml
3-o-ETHYL ASCORBIC ACID 0.1%/ml

INACTIVE INGREDIENT

WATER
GLYCERIN
PROPYLENE GLYCOL
CAPRYLIC/CAPRIC TRIGLYCERIDE
CETEARYL ALCOHOL
CETEARYL GLUCOSIDE
DIMETHICONE 350
BUTYROSPERMUM PARKII (SHEA) BUTTER
GLYCERYL STEARATE
PORTULACA OLERACEA EXTRACT
CHRYSANTHELLUM INDICUM EXTRACT
PELARGONIUM GRAVEOLENS EXTRACT
MENTHA ARVENSIS LEAF EXTRACT
ALOE BARBADENSIS EXTRACT
SOPHORA ANGUSTIFOLIA ROOT EXTRACT
SQUALANE
TOCOPHERYL ACETATE
1,2-HEXANEDIOL
HYDROXYACETOPHENONE
PHENOXYETHANOL
ETHYLHEXYLGLYCERIN
CARBOMER
DISODIUM EDTA
FRAGRANCE

PURPOSE

DARK SPOT REMOVERFOR FACE AND BODY:Deeply hydrates the skinReduces uneven skin toneMinimizes age spots,sun spots, freckles,brown spots, etc.Firms skin, improveselasticity and firmness.

WARNINGS

WARNINGSThis product is forexternal use only andshould not come intocontact with the eyes.In case of inadvertentcontact, rinse immediatelywith water and seekmedical attention. lfyou have allergicsymptoms or skinabnormalities,pleasestop using and seekmedical advice

STOP USE

If pregnant or breast-feading, ask a heatthprofessional before use, Keep out of reach ofchildren, in case of overdose,got medical help orcontact a Poison Control Center right away.

DO NOT USE

When using this productuSwipe onto a clean face, morning and/or evening. Do not rinse. For daytime use, follow with sunscreen

KEEP OUT OF REACH OF CHILDREN

keep out of reach ofchildren.In case of overdose,got medical helpor contact a Poison Control Center right away

INDICATIONS AND USAGE

INSTRUCTIONS
Step 1: Wash your faceand keep it clean.
Step 2: Take an appropriateamount of dark spotcream and apply evenly to the desiredarea, massage gentlyfor 1-2 minutes.
Step 3: Use twice a day, with massage to help absorption, adhere to the use of more than a month the best results.
It is recommended to use it twice a day inthe morning andevening for both menand women.

DOSAGE AND ADMINISTRATION

Take an appropriateamount of dark spotcream and apply evenly to the desiredarea, massage gentlyfor 1-2 minutes.

When using this product#Swipe onto a clean face, morning and/or evening.Do not rinse.
. For daytime use, follow with sunscreen